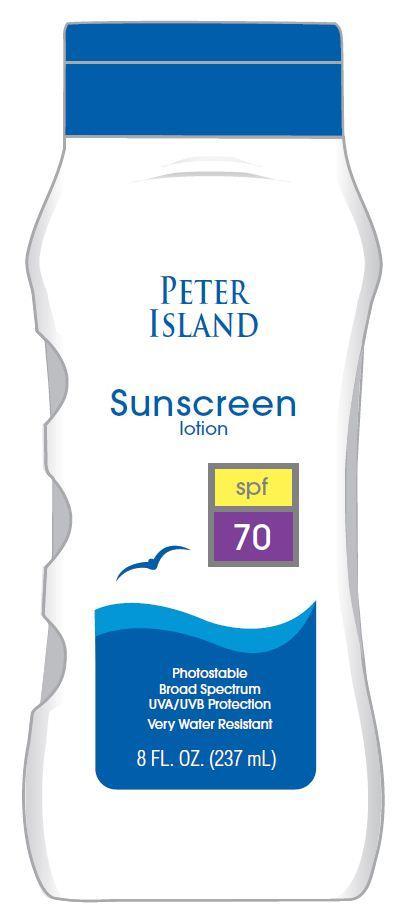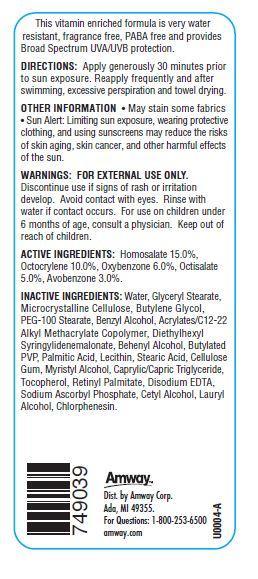 DRUG LABEL: Peter Island Sunscreen
NDC: 10056-704 | Form: LOTION
Manufacturer: Access Business Group LLC
Category: otc | Type: HUMAN OTC DRUG LABEL
Date: 20130628

ACTIVE INGREDIENTS: HOMOSALATE 15 g/100 g; OXYBENZONE 6 g/100 g; AVOBENZONE 3 g/100 g; OCTISALATE 5 g/100 g; OCTOCRYLENE 10 g/100 g
INACTIVE INGREDIENTS: WATER; GLYCERYL MONOSTEARATE; CELLULOSE, MICROCRYSTALLINE; DIETHYLHEXYL SYRINGYLIDENEMALONATE; DOCOSANOL; PALMITIC ACID; CARBOXYMETHYLCELLULOSE SODIUM; MYRISTYL ALCOHOL; EDETATE DISODIUM; SODIUM ASCORBYL PHOSPHATE; CETYL ALCOHOL; LAURYL ALCOHOL; CHLORPHENESIN; PEG-100 STEARATE; STEARIC ACID; TRICAPRIN; TOCOPHEROL; VITAMIN A PALMITATE

ACTIVE INGREDIENTS:

Homosalate 15.0%

Octocrylene 10.0%

Oxybenzone 6.0%

Octisalate 5.0%

Avobenzone 3.0%

WARNING:

FOR EXTERNAL USE ONLY.
Avoid contact with eyes. Rinse with water if contact occurs.

STOP USE

Discontinue use if signs of rash or irritation develop.

ASK DOCTOR

For use on children under the age of 6 months consult a physician.

Keep out of reach of children.

DIRECTIONS:

Apply generously and evenly 30 minutes before sun exposure. Reapply frequently and after swimming, excessive perspiration and towel drying.

OTHER INFORMATION

- May stain some fabrics
- Sun Alert: Limiting sun exposure, wearing protective clothing, and using sunscreens may reduce the risks of skin aging, skin cancer, and other harmful effects of the sun.

This vitamin enriched formula is very water resistant, fragrance free, PABA free and provides Broad Spectrum UVA/UVB protection.

Principal Display Panel

PETER ISLAND

Sunscreen lotion

spf 70

Photostable

Broad Spectrum

UVA/UVB Protection

Very Water Resistant

8 FL.OZ. (237 mL)

INACTIVE INGREDIENTS:

Water, Glyceryl Stearate, Microcrystalline Cellulose, Butylene Glycol, PEG-100 Stearate, Acrylates/C12-22 Alkyl Methacrylate Copolymer, Benzyl Alcohol, Diethylhexyl Syringylidenemalonate, Behenyl Alcohol, Butylated PVP, Palmitic Acid, Stearic Acid, C12-16 Alcohols, Cellulose Gum, Caprylic/Capric Triglyceride, Lecithin, Retinyl Palmitate, Tocopherol, Sodium Ascorbyl Phosphate, Disodium EDTA, Chlorphenesin.